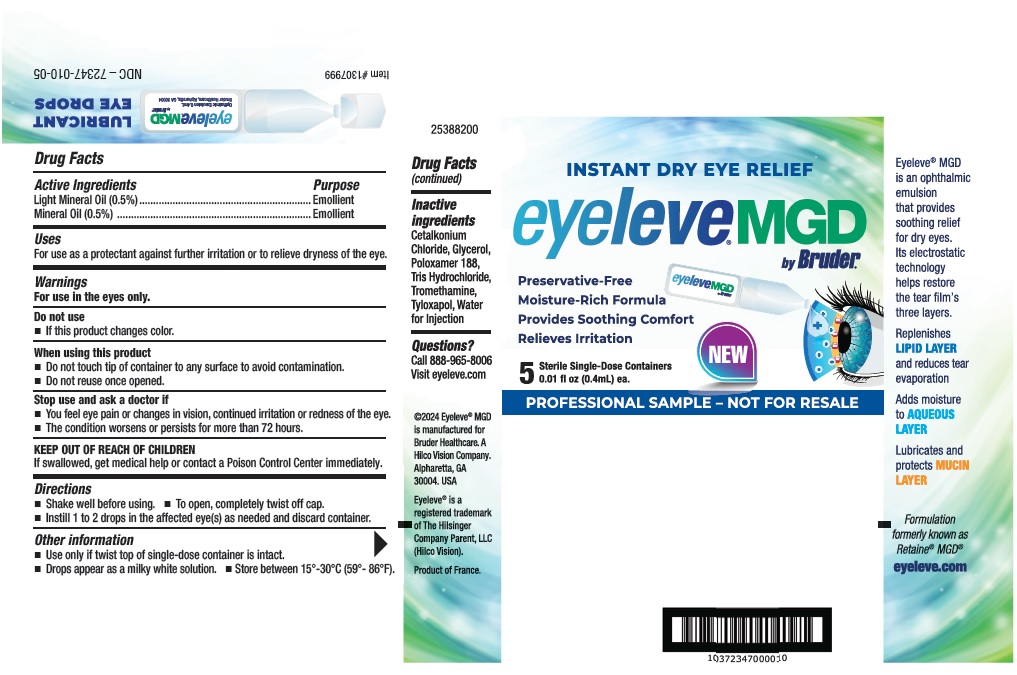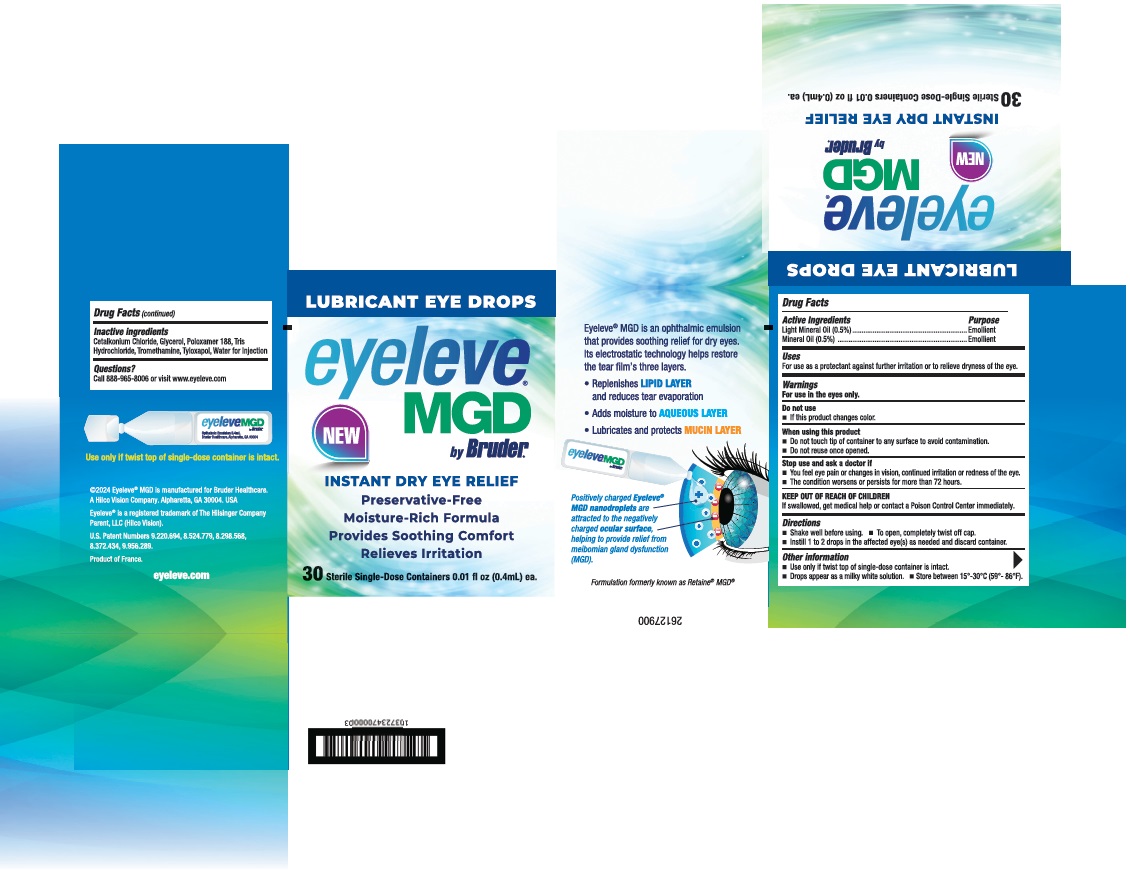 DRUG LABEL: Eyeleve MGD
NDC: 72347-010 | Form: EMULSION
Manufacturer: Bruder Healthcare
Category: otc | Type: HUMAN OTC DRUG LABEL
Date: 20250715

ACTIVE INGREDIENTS: LIGHT MINERAL OIL 2 mg/0.4 mL; MINERAL OIL 2 mg/0.4 mL
INACTIVE INGREDIENTS: CETALKONIUM CHLORIDE; GLYCERIN; POLOXAMER 188; TROMETHAMINE HYDROCHLORIDE; TROMETHAMINE; TYLOXAPOL; WATER

Drug Facts

Active Ingredients Purpose

Light Mineral Oil (0.5%)............................Emollient

Mineral Oil (0.5%)......................................Emollient

Uses

For use as a protectant against further irritation or to relieve dryness of the eye.

Warnings

For use in the eyes only.

Do not use

- If this product changes color.

When using this product

- Do not touch tip of container to any surface to avoid contamination.
- Do not reuse once opened.

Stop use and ask a doctor if

- You feel eye pain or changes in vision, continued irritation or redness of the eye.
- The condition worsens or persists for more than 72 hours.

KEEP OUT OF REACH OF CHILDREN

If swallowed, get medical help or contact a Poison Control Center immediately.

Directions

- Shake well before using.
- To open, completely twist off cap.
- Instill 1 to 2 drops in the affected eye(s) as needed and discard container.

Other information

- Use only if twist top of single-dose container is intact.
- Drops appear as a milky white solution.
- Store between 15°-30°C (59°- 86°F).

Inactive ingredients

Cetalkonium Chloride, Glycerol, Poloxamer 188, Tris Hydrochloride, Tromethamine, Tyloxapol, Water for Injection

Questions?

Call 888-965-8006 or visit www.eyeleve.com

PRINCIPAL DISPLAY PANEL - 5 Sterile Single-Dose Containers

NDC – 72347-010-05

INSTANT DRY EYE RELIEF

eyeleve®MGD
by Bruder®

NEW

Preservative-Free
Moisture-Rich Formula
Provides Soothing Comfort
Relieves Irritation

5 Sterile Single-Dose Containers
0.01 fl oz (0.4mL) ea.

PROFESSIONAL SAMPLE – NOT FOR RESALE

PRINCIPAL DISPLAY PANEL - 30 Sterile Single-Dose Containers

NDC 72347-010-30

LUBRICANT EYE DROPS

eyeleve®
MGD
by Bruder®

NEW

INSTANT DRY EYE RELIEF

Preservative-Free
Moisture-Rich Formula
Provides Soothing Comfort
Relieves Irritation

30 Sterile Single-Dose Containers 0.01 fl oz (0.4mL) ea.